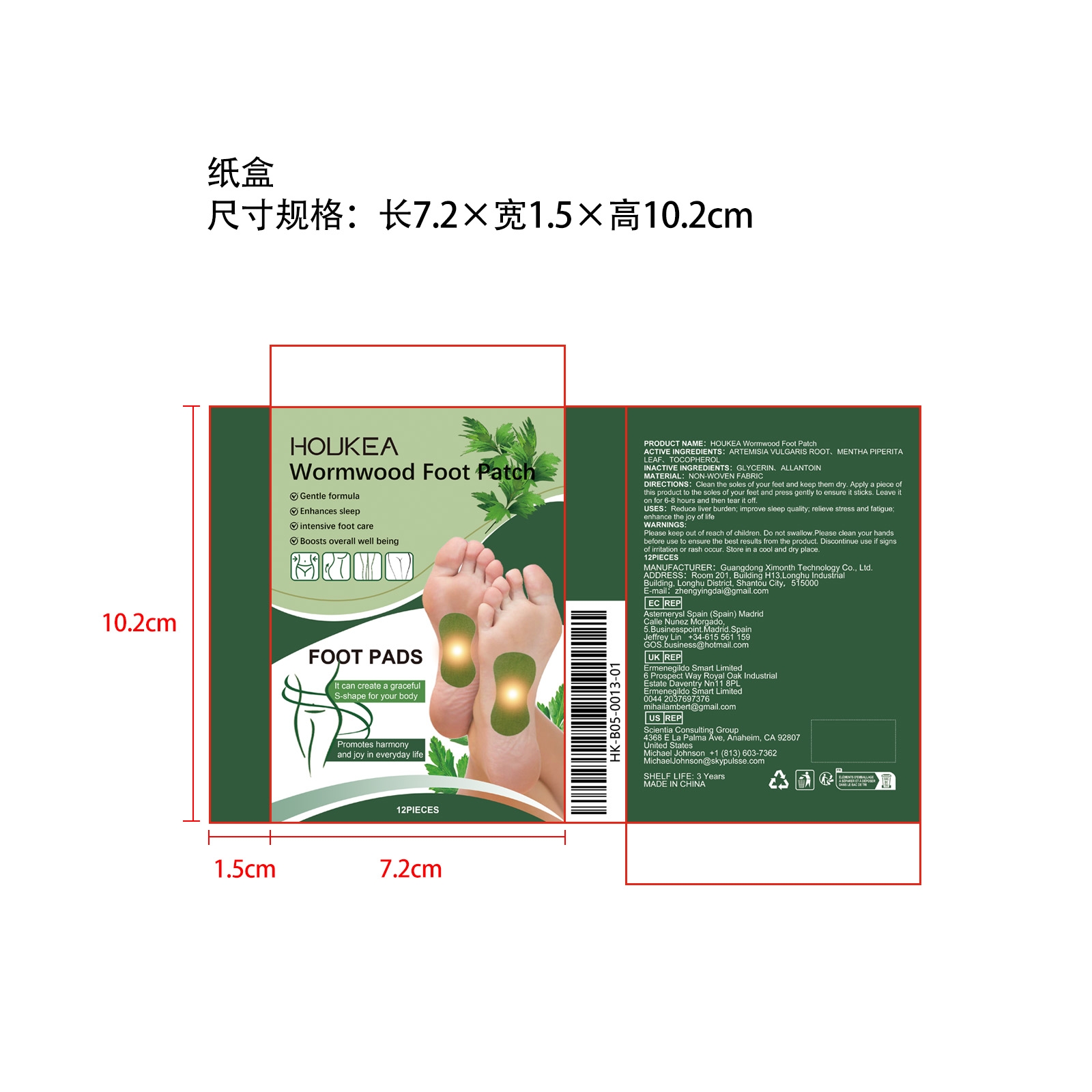 DRUG LABEL: HOUKEA Wormwood Foot Patch
NDC: 84660-099 | Form: PATCH
Manufacturer: Guangdong Ximonth Technology Co., Ltd.
Category: otc | Type: HUMAN OTC DRUG LABEL
Date: 20241031

ACTIVE INGREDIENTS: MENTHA PIPERITA LEAF 2 mg/12 mg; ARTEMISIA VULGARIS ROOT 2 mg/12 mg; TOCOPHEROL 4 mg/12 mg
INACTIVE INGREDIENTS: GLYCERIN 2 mg/12 mg; ALLANTOIN 2 mg/12 mg

Active Ingredient(s)

ARTEMISIA VULGARIS ROOT、MENTHA PIPERITA LEAF、TOCOPHEROL

Purpose

Reduce liver burden; improve sleep quality; relieve stress and fatigue; enhance the joy of life

Use

Clean the soles of your feet and keep them dry. Apply a piece of this product to the soles of your feet and press gently to ensure it sticks. Leave it on for 6-8 hours and then tear it off.

Warnings

Please keep out of reach of children.Do not swallow.Please clean your hands before use to ensure the best results from the product.Discontinue use if signs of irritation or rash occur.Store in a cool and dry place.

Do not use

Discontinue use if signs of irritation or rash occur.

Stop Use

Discontinue use if signs of irritation or rash occur.

KEEP OUT OF REACH OF CHILDREN

Please keep out of reach of children. Do not swallow.

STORAGE AND HANDLING

Store in a cool and dry place.

INACTIVE INGREDIENT

GLYCERIN、ALLANTOIN